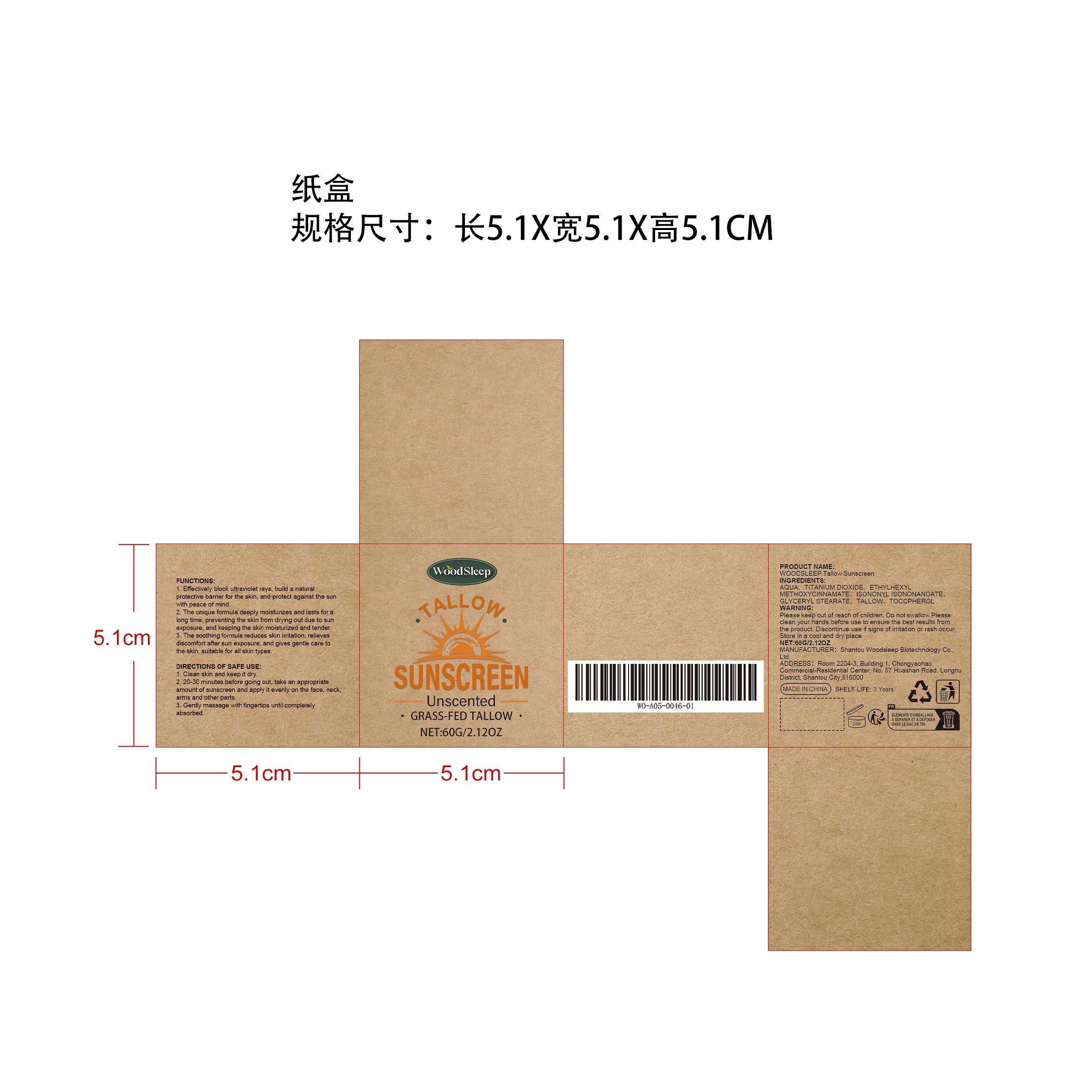 DRUG LABEL: WOODSLEEP Tallow Sunscreen
NDC: 85053-003 | Form: CREAM
Manufacturer: Shantou Woodsleep Biotechnology Co., Ltd.
Category: otc | Type: HUMAN OTC DRUG LABEL
Date: 20251126

ACTIVE INGREDIENTS: TALLOW 0.012 mg/60 mg
INACTIVE INGREDIENTS: ISONONYL ISONONANOATE 2.4 mg/60 mg; TOCOPHEROL 0.012 mg/60 mg; TITANIUM DIOXIDE 15 mg/60 mg; GLYCERYL STEARATE 1.2 mg/60 mg; AQUA 35.976 mg/60 mg; ETHYLHEXYL METHOXYCINNAMATE 5.4 mg/60 mg

WHEN USING

1. Clean skin and keep it dry.

2. 20-30 minutes before going out, take an appropriate amount of sunscreen and apply it evenly on the face, neck, arms and other parts.

3. Gently massage with fingertips until completely absorbed.

PURPOSE

1. Effectively block ultraviolet rays, build a natural protective barrier for the skin, and protect against the sun with peace of mind.

2. The unique formula deeply moisturizes and lasts for a long time, preventing the skin from drying out due to sun exposure, and keeping the skin moisturized and tender.

3. The soothing formula reduces skin irritation, relieves discomfort after sun exposure, and gives gentle care to the skin, suitable for all skin types.

DO NOT USE

Discontinue use if signs of irritation or rash occur.

STOP USE

Discontinue use if signs of irritation or rash occur.

KEEP OUT OF REACH OF CHILDREN

Please keep out of reach of children. Do not swallow.

WARNINGS

Please keep out of reach of children. Do not swallow.Please clean your hands before use to ensure the best results from the product. Discontinue use if signs of irritation or rash occur. Store in a cool and dry place.

STORAGE AND HANDLING

Store in a cool and dry place.

INACTIVE INGREDIENT

AQUA、TITANIUM DIOXIDE、ETHYLHEXYL METHOXYCINNAMATE、ISONONYL ISONONANOATE、GLYCERYL STEARATE、TOCOPHEROL

ACTIVE INGREDIENT

TALLOW